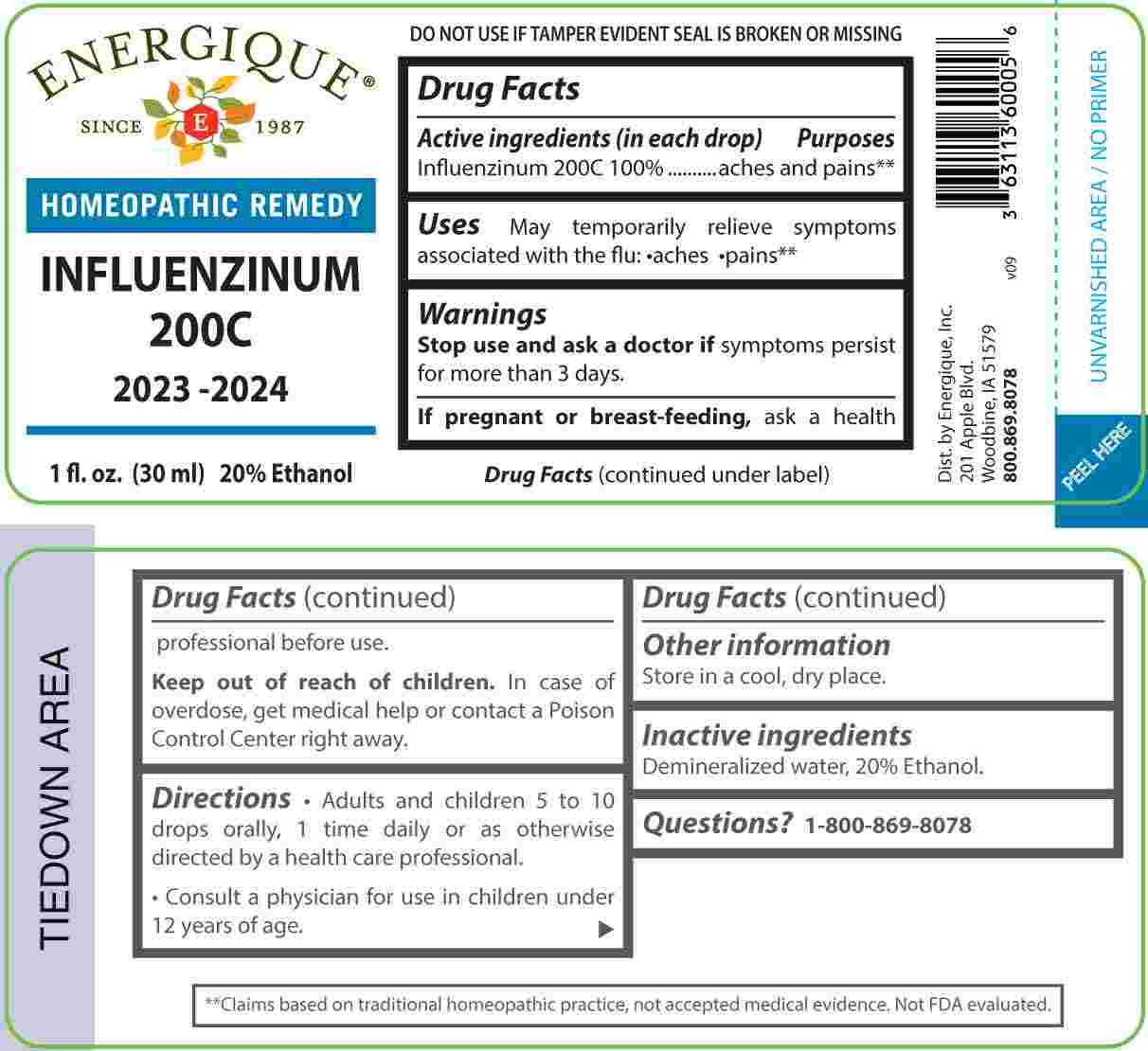 DRUG LABEL: Influenzinum 200C
NDC: 44911-0705 | Form: LIQUID
Manufacturer: Energique, Inc.
Category: homeopathic | Type: HUMAN OTC DRUG LABEL
Date: 20250516

ACTIVE INGREDIENTS: INFLUENZA A VIRUS WHOLE 200 [hp_C]/1 mL; INFLUENZA A VIRUS A/DARWIN/6/2021 (H3N2) WHOLE 200 [hp_C]/1 mL; INFLUENZA B VIRUS B/AUSTRIA/1359417/2021 BVR-26 WHOLE 200 [hp_C]/1 mL; INFLUENZA B VIRUS B/PHUKET/3073/2013 BVR-1B WHOLE 200 [hp_C]/1 mL
INACTIVE INGREDIENTS: WATER; ALCOHOL

DRUG FACTS:

ACTIVE INGREDIENT:

(in each drop) Influenzinum 200C 100%.

PURPOSES:

Influenzinum 200C - aches and pains.**

**Claims based on traditional homeopathic practice, not accepted medical evidence. Not FDA evaluated.

USES:

May temporarily relieve symptoms associated with the flu: • aches • pains.**

**Claims based on traditional homeopathic practice, not accepted medical evidence. Not FDA evaluated.

WARNINGS:

Stop use and ask a doctor if symptoms persist for more than 3 days.

If pregnant or breastfeeding, ask a health professional before use.

Keep out of reach of children. In case of overdose, get medical help or contact a Poison Control Center right away.

DO NOT USE IF TAMPER EVIDENT SEAL IS BROKEN OR MISSING.

Store in a cool, dry place.

KEEP OUT OF REACH OF CHILDREN:

In case of overdose, get medical help or contact a Poison Control Center right away.

DIRECTIONS:

• Adults and children 5 to 10 drops orally, 1 time daily or as otherwise directed by a health care professional.

• Consult a physician for use in children under 12 years of age.

INACTIVE INGREDIENTS:

Demineralized water, 20% Ethanol.

QUESTIONS:

Dist. by Energique, Inc.
201 Apple Blvd.
Woodbine, IA 51579

800.869.8078

PACKAGE LABEL DISPLAY:

ENERGIQUE

SINCE 1987

HOMEOPATHIC REMEDY

INFLUENZINUM
200C
2023-2024

1 fl. oz. (30 ml)